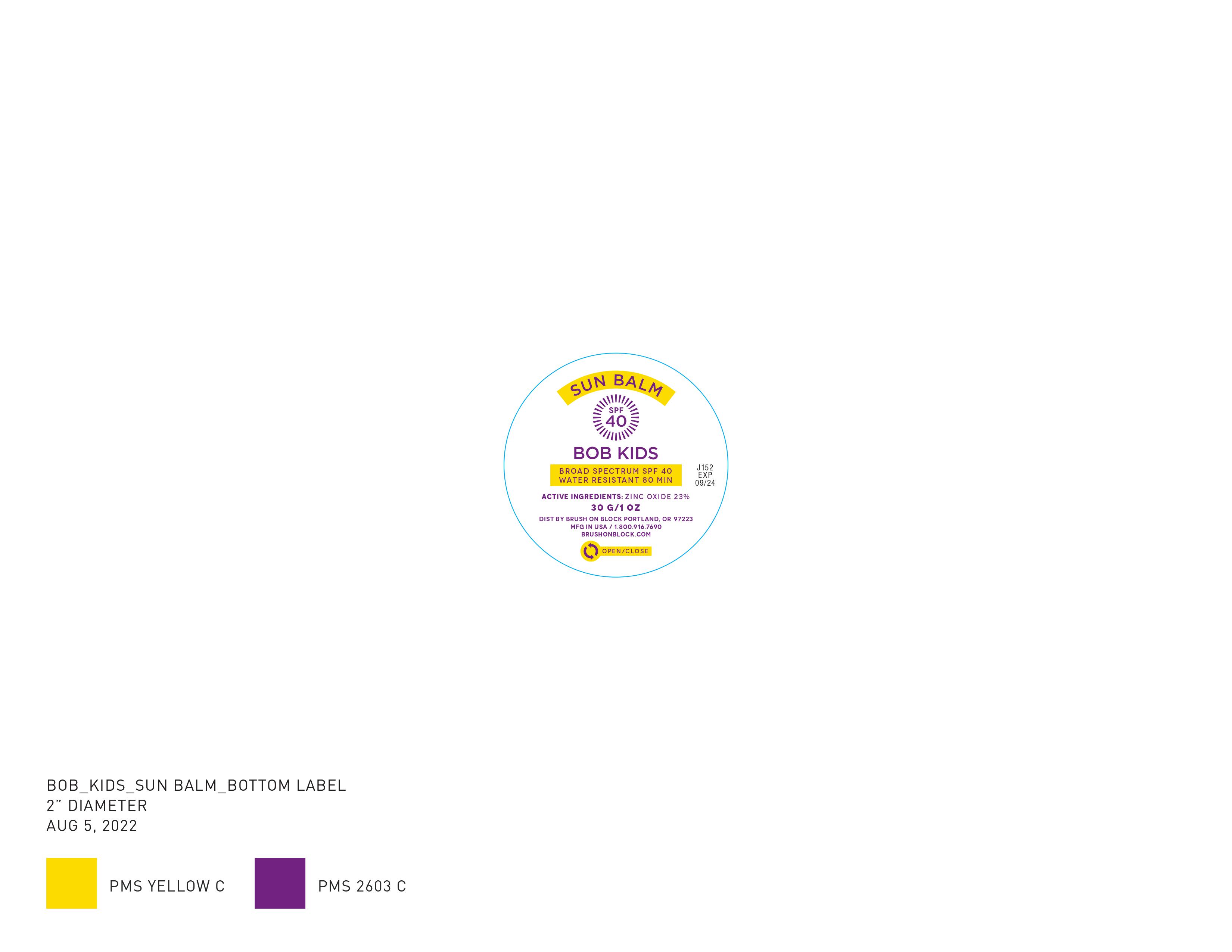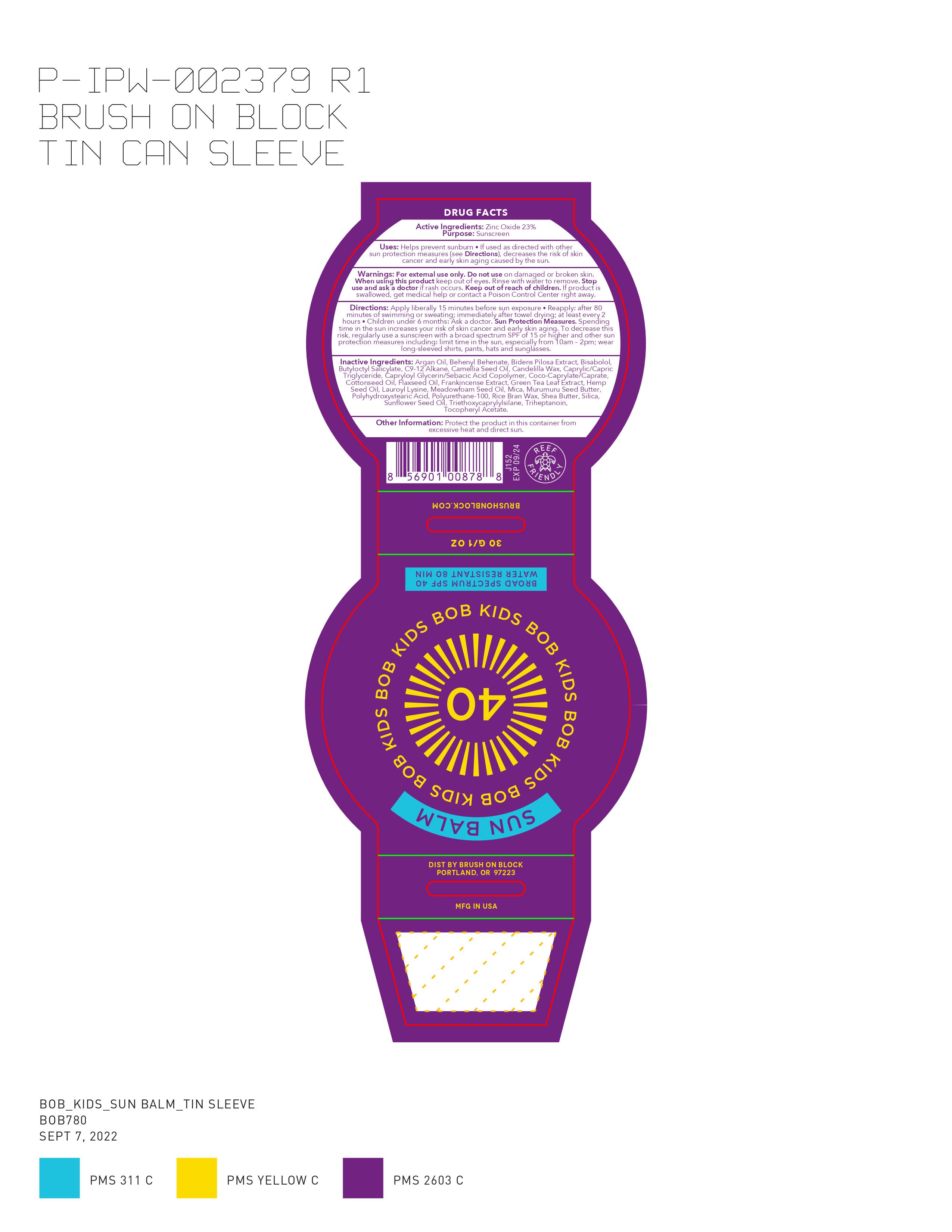 DRUG LABEL: BOB Kids Sun Balm SPF 40
NDC: 58274-009 | Form: CREAM
Manufacturer: SPF Ventures, LLC
Category: otc | Type: HUMAN OTC DRUG LABEL
Date: 20250824

ACTIVE INGREDIENTS: ZINC OXIDE 23 g/100 g
INACTIVE INGREDIENTS: ARGAN OIL; INDIAN FRANKINCENSE; SHEA BUTTER; LEVOMENOL; ASTROCARYUM MURUMURU SEED BUTTER; BEHENYL BEHENATE; BIDENS PILOSA LEAF; BUTYLOCTYL SALICYLATE; CAMELLIA OLEIFERA SEED; CANDELILLA WAX; SUNFLOWER OIL; MEADOWFOAM SEED OIL; RICE BRAN; POLYHYDROXYSTEARIC ACID STEARATE; SILICON DIOXIDE; TRIETHOXYCAPRYLYLSILANE; TRIHEPTANOIN; LEVANT COTTONSEED OIL; CAPRYLOYL GLYCERIN/SEBACIC ACID COPOLYMER (2000 MPA.S); COCO-CAPRYLATE/CAPRATE; LAUROYL LYSINE; COCONUT ALKANES; CANNABIS SATIVA SEED OIL; MEDIUM-CHAIN TRIGLYCERIDES; LINSEED OIL; MICA

BOB Kids Sun Balm SPF 40

Active Ingredients

Zinc Oxide 23%

Purpose

Sunscreen

Uses

- Helps prevent sunburn
- if used as directed with other sun protection measures (see Directions), decreases the risk of skin cancer and early aging caused by the sun.

Warnings

For external use only

Do not use

on damaged or broken skin.

When using this product

keep out of eyes. Rinse with water to remove.

Stop use and ask a doctor

if rash occurs.

Keep out of reach of children.

If product is swallowed, get medical help or contact a Poison Control Center right away.

Directions

- Apply liberally 15 minutes before sun exposure
- Reapply: after 80 minutes of swimming or sweating; immediately after towel drying; at least every 2 hours
- Children under 6 months: Ask a doctor.
- Sun Protection Measures. Spending time in the sun increases your risk of skin cancer and early skin aging. To decrease this risk, regularly use a sunscreen with a broad spectrum SPF of 15 or higher and other sun protection measures including: limit time in the sun, especially from 10 a.m. - 2 p.m., wear long-sleeve shirts, pants, hats, and sunglasses.

Inactive Ingredients

Argan Oil, Behenyl Behenate, Bidens Pilosa Extract, Bisabolol, Butyloctyl Salicylate, C9-12 Alkane, Camellia Seed Oil, Candelilla Wax, Caprylic/Capric Triglyceride, Capryloyl Glycerin/Sebacic Acid Copolymer, Coco-Caprylate/Caprate, Cottonseed Oil, Flaxseed Oil, Frankincense Extract, Green Tea Leaf Extract, Hemp Seed Oil, Lauroyl Lysine, Meadowfoam Seed Oil, Mica, Murumuru Seed Butter, Polyhydroxystearic Acid, Polyurethane-100, Rice Bran Wax, Shea Butter, Silica, Sunflower Seed Oil, Triethoxycaprylylsilane, Triheptanoin, Tocopheryl Acetate.

Other Information

Protect the product in this container from excessive heat and direct sun.

QUESTIONS

MFG in USA / 1.800.916.7690